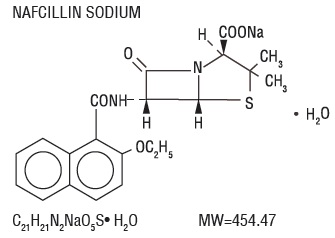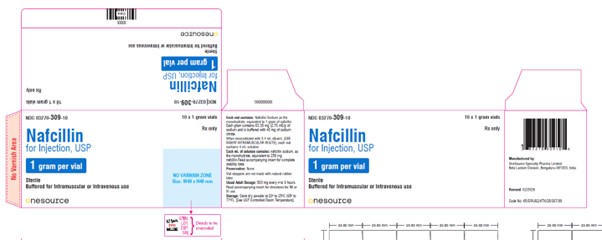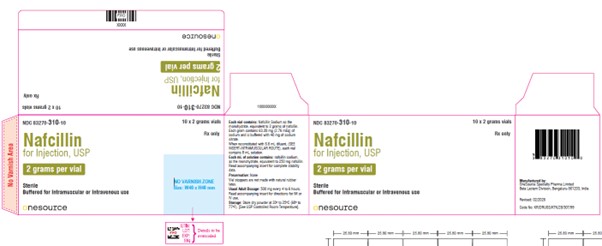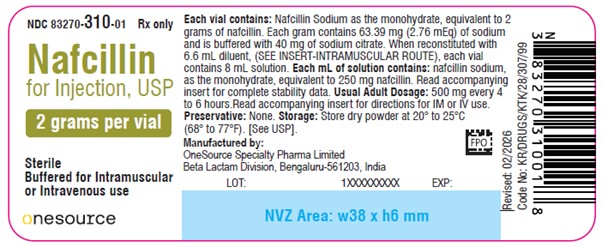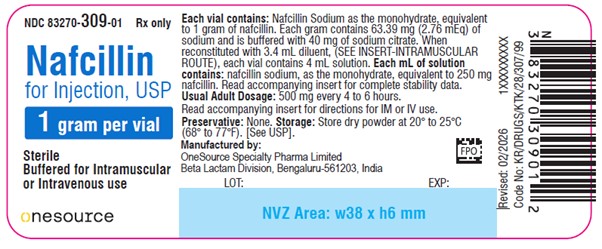 DRUG LABEL: NAFCILLIN SODIUM
NDC: 83270-309 | Form: INJECTION, POWDER, FOR SOLUTION
Manufacturer: ONESOURCE SPECIALTY PHARMA LIMITED
Category: prescription | Type: HUMAN PRESCRIPTION DRUG LABEL
Date: 20260220

ACTIVE INGREDIENTS: NAFCILLIN SODIUM 2 g/1 1
INACTIVE INGREDIENTS: SODIUM CITRATE

Nafcillin for Injection, USP
For Intramuscular or Intravenous Injection

Rx only

To reduce the development of drug-resistant bacteria and maintain the effectiveness of Nafcillin for Injection and other antibacterial drugs, Nafcillin for Injection should be used only to treat or prevent infections that are proven or strongly suspected to be caused by bacteria.

DESCRIPTION

Nafcillin for Injection, USP is semisynthetic penicillin derived from the penicillin nucleus, 6-aminopenicillanic acid. The chemical name of nafcillin sodium is Monosodium (2 S,5 R,6 R)-6-(2-ethoxy-1-naphthamido)-3,3-dimethyl-7-oxo-4-thia-1-azabicyclo[3.2.0]heptane-2-carboxylatemonohydrate. It is resistant to inactivation by the enzyme penicillinase (beta-lactamase). The structural formula is as follows:

Nafcillin for Injection, USP for the intramuscular or intravenous route of administration, contains nafcillin sodium as a sterile white to yellowish white powder for reconstitution. The pH of the reconstituted solution is 6 to 8.5. Nafcillin for Injection, USP contains nafcillin sodium as the monohydrate equivalent to 1 gram or 2 grams of nafcillin per vial and is buffered with 40 mg sodium citrate per gram. The sodium content is 63.39 mg [2.76 mEq] per gram.

CLINICAL PHARMACOLOGY

In a study of five healthy adults administered a single 500 mg dose of nafcillin by intravenous injection over seven minutes, the mean plasma concentration of the drug was approximately 30 mcg/mL at 5 minutes after injection. The mean area under the plasma concentration-versus-time curve (AUC) for nafcillin in this study was 18.06 mcg.h/mL.

The serum half-life of nafcillin administered by the intravenous route ranged from 33 to 61 minutes as measured in three separate studies.

In contrast to the other penicillinase-resistant penicillins, only about 30% of nafcillin is excreted as unchanged drug in the urine of normal volunteers, and most within the first six hours. Nafcillin is primarily eliminated by nonrenal routes, namely hepatic inactivation and excretion in the bile.

Nafcillin binds to serum proteins, mainly albumin. The degree of protein binding reported for nafcillin is 89.9 ± 1.5%. Reported values vary with the method of study and the investigator.

The concurrent administration of probenecid with nafcillin increases and prolongs plasma concentrations of nafcillin. Probenecid significantly reduces the total body clearance of nafcillin with renal clearance being decreased to a greater extent than nonrenal clearance.

The penicillinase-resistant penicillins are widely distributed in various body fluids, including bile, pleural, amniotic and synovial fluids. With normal doses insignificant concentrations are found in the aqueous humor of the eye. High nafcillin CSF levels have been obtained in the presence of inflamed meninges.

Renal failure does not appreciably affect the serum half-life of nafcillin; therefore, no modification of the usual nafcillin dosage is necessary in renal failure with or without hemodialysis. Hemodialysis does not accelerate the rate of clearance of nafcillin from the blood.

A study which assessed the effects of cirrhosis and extrahepatic biliary obstruction in man demonstrated that the plasma clearance of nafcillin was significantly decreased in patients with hepatic dysfunction. In these patients with cirrhosis and extrahepatic obstruction, nafcillin excretion in the urine was significantly increased from about 30 to 50% of the administered dose, suggesting that renal disease superimposed on hepatic disease could further decrease nafcillin clearance.

PHARMACOKINETICS

Intramuscular injections of nafcillin sodium, USP 1 gram produced peak serum levels in 0.5 to 1 hour of 7.61 mcg/mL. The degree of protein binding reported has been 89.9 +/-1.5%. With normal doses nafcillin is found in therapeutic concentrations in the pleural, bile, and amniotic fluids. Insignificant concentrations are found in the cerebrospinal fluid and aqueous humor. Blood concentrations may be tripled by the concurrent use of probenecid. Clinical studies with nafcillin sodium in infants under three days of age and prematures have revealed higher blood levels and slower rates of urinary excretion than in older children and adults. A high concentration of nafcillin sodium is excreted via the bile. About 30% of an intramuscular dose is excreted in the urine.

MICROBIOLOGY

Penicillinase-resistant penicillins exert a bactericidal action against penicillin-susceptible microorganisms during the state of active multiplication. All penicillins inhibit the biosynthesis of the bacterial cell wall. Nafcillin sodium has been shown to be active against most isolates of the following microorganism, both in vitroand in clinical infections as described in the INDICATIONS AND USAGE section.

Gram-Positive Bacteria

Staphylococcus aureus(Methicillin-susceptible isolates only)

Susceptibility Test Methods

For specific information regarding susceptibility test interpretive criteria, and associated test methods and quality control standards recognized by FDA for nafcillin for injection, please see: https://www.fda.gov/STIC.

INDICATIONS AND USAGE

Nafcillin is indicated in the treatment of infections caused by penicillinase-producing staphylococci which have demonstrated susceptibility to the drug. Culture and susceptibility tests should be performed initially to determine the causative organism and its susceptibility to the drug (see CLINICAL PHARMACOLOGY— Susceptibility Test Methods.

Nafcillin should not be used in infections caused by organisms susceptible to penicillin G. If the susceptibility tests indicate that the infection is due to methicillin-resistant Staphylococcus sp.,therapy with Nafcillin for Injection, USP should be discontinued and alternative therapy provided.

To reduce the development of drug-resistant bacteria and maintain the effectiveness of Nafcillin for Injection, USP and other antibacterial drugs, Nafcillin for Injection, USP should be used only to treat or prevent infections that are proven or strongly suspected to be caused by susceptible bacteria. When culture and susceptibility information are available, they should be considered in selecting or modifying antibacterial therapy. In the absence of such data, local epidemiology and susceptibility patterns may contribute to the empiric selection of therapy.

CONTRAINDICATIONS

A history of a hypersensitivity (anaphylactic) reaction to any penicillin is a contraindication.

WARNINGS

Serious and occasionally fatal hypersensitivity (anaphylactic) reactions have been reported in patients on penicillin therapy. These reactions are more likely to occur in individuals with a history of penicillin hypersensitivity and/or a history of sensitivity to multiple allergens. Before initiating therapy with Nafcillin, careful inquiry should be made concerning previous hypersensitivity reactions to penicillins, cephalosporins, or other allergens. If an allergic reaction occurs, Nafcillin should be discontinued and appropriate therapy instituted.

Clostridium difficile associated diarrhea (CDAD) has been reported with use of nearly all antibacterial agents, including Nafcillin for Injection, USP, and may range in severity from mild diarrhea to fatal colitis. Treatment with antibacterial agents alters the normal flora of the colon leading to overgrowth of C. difficile.

C. difficile produces toxins A and B which contribute to the development of CDAD. Hypertoxin producing strains of C. difficile cause increased morbidity and mortality, as these infections can be refractory to antimicrobial therapy and may require colectomy. CDAD must be considered in all patients who present with diarrhea following antibiotic use. Careful medical history is necessary since CDAD has been reported to occur over two months after the administration of antibacterial agents.

If CDAD is suspected or confirmed, ongoing antibiotic use not directed against C. difficile may need to be discontinued. Appropriate fluid and electrolyte management, protein supplementation, antibiotic treatment of C. difficile, and surgical evaluation should be instituted as clinically indicated.

PRECAUTIONS

General

Nafcillin should generally not be administered to patients with a history of sensitivity to any penicillin.

Penicillin should be used with caution in individuals with histories of significant allergies and/or asthma. Whenever allergic reactions occur, penicillin should be withdrawn unless, in the opinion of the physician, the condition being treated is life-threatening and amenable only to penicillin therapy. The use of antibiotics may result in overgrowth of nonsusceptible organisms. If new infections due to bacteria or fungi occur, the drug should be discontinued and appropriate measures taken.

The liver/biliary tract is the primary route of nafcillin clearance. Caution should be exercised when patients with concomitant hepatic insufficiency and renal dysfunction are treated with nafcillin.

Prescribing Nafcillin for Injection in the absence of a proven or strongly suspected bacterial infection or a prophylactic indication is unlikely to provide benefit to the patient and increases the risk of the development of drug-resistant bacteria.

Laboratory Tests

Bacteriologic studies to determine the causative organisms and their susceptibility to the penicillinase-resistant penicillins should be performed (See CLINICAL PHARMACOLOGY- MICROBIOLOGY). In the treatment of suspected staphylococcal infections, therapy should be changed to another active agent if culture tests fail to demonstrate the presence of staphylococci.

Periodic assessment of organ system function including renal, hepatic, and hematopoietic should be made during prolonged therapy with nafcillin. White blood cell and differential cell counts should be obtained prior to initiation of therapy and periodically during therapy with nafcillin. Urinalysis, serum blood urea nitrogen, and creatinine determinations should be performed at baseline and during therapy with nafcillin. Serum bilirubin, SGOT, SGPT, alkaline phosphatase, and gamma glutamyl transferase should be obtained at baseline and periodically during therapy, especially when using high nafcillin doses. In patients with worsening hepatic function, the risk versus benefit of continued nafcillin use should be re-evaluated.

Drug Interactions

Tetracycline, a bacteriostatic antibiotic, may antagonize the bactericidal effect of penicillin, and concurrent use of these drugs should be avoided.

Nafcillin in high dosage regimens, i.e ., 2 grams every 4 hours, has been reported to decrease the effects of warfarin. When nafcillin and warfarin are used concomitantly, the prothrombin time should be closely monitored and the dose of warfarin adjusted as necessary. This effect may persist for up to 30 days after nafcillin has been discontinued.

Nafcillin when administered concomitantly with cyclosporine has been reported to result in subtherapeutic cyclosporine levels. The nafcillin-cyclosporine interaction was documented in a patient during two separate courses of therapy. When cyclosporine and nafcillin are used concomitantly in organ transplant patients, the cyclosporine levels should be monitored.

Drug/Laboratory Test Interactions

Nafcillin in the urine can cause a false-positive urine reaction for protein when the sulfosalicyclic acid test is used, but not with the dipstick.

Carcinogenesis, Mutagenesis, Impairment of Fertility

No long term animal studies have been conducted with these drugs. Studies on reproduction (nafcillin) in rats and mice reveal no fetal or maternal abnormalities before conception and continuously through weaning (one generation).

Pregnancy

Teratogenic Effects

Reproduction studies have been performed in the mouse with oral doses up to 20 times the human dose and orally in the rat at doses up to 40 times the human dose and have revealed no evidence of impaired fertility or harm to the rodent fetus due to nafcillin. There are, however, no adequate or well- controlled studies in pregnant women. Because animal reproduction studies are not always predictive of human response, nafcillin should be used during pregnancy only if clearly needed.

Nursing Mothers

Penicillins are excreted in human milk. Caution should be exercised when penicillins are administered to a nursing woman.

Pediatric Use

The liver/biliary tract is the principal route of nafcillin elimination. Because of immature hepatic and renal function in pediatric patients, nafcillin excretion may be impaired. Safety and effectiveness in pediatric patients have not been established for the use of intravenous nafcillin. Safety and effectiveness in pediatric patients have been established for the use of intramuscular nafcillin.

Geriatric Use

Clinical studies of Nafcillin for Injection did not include sufficient numbers of subjects aged 65 and over to determine whether they respond differently from younger subjects. Other reported clinical experience has not identified differences in responses between the elderly and younger patients. In general, dose selection for an elderly patient should be cautious, usually starting at the low end of the dosing range, reflecting the greater frequency of decreased hepatic, renal, or cardiac function, and of concomitant disease or other drug therapy.

Nafcillin for Injection contains 63.39 mg [2.76 mEq] of sodium per gram. At the usual recommended doses, patients would receive between 126.8 and 380.3 mg/day (5.52 and 16.56 mEq) of sodium. The geriatric population may respond with a blunted natriuresis to salt loading. This may be clinically important with regard to such diseases as congestive heart failure.

Information for Patients

Patients should be counseled that antibacterial drugs including Nafcillin for Injection should only be used to treat bacterial infections. They do not treat viral infections (e.g., the common cold). When Nafcillin for Injection is prescribed to treat a bacterial infection, patients should be told that although it is common to feel better early in the course of therapy, the medication should be taken exactly as directed. Skipping doses or not completing the full course of therapy may (1) decrease the effectiveness of the immediate treatment and (2) increase the likelihood that bacteria will develop resistance and will not be treatable by Nafcillin for Injection or other antibacterial drugs in the future.

Diarrhea is a common problem caused by antibiotics which usually ends when the antibiotic is discontinued. Sometimes after starting treatment with antibiotics, patients can develop watery and bloody stools (with or without stomach cramps and fever) even as late as two or more months after having taken the last dose of the antibiotic. If this occurs, patients should contact their physician as soon as possible.

ADVERSE REACTIONS

Body as a Whole

The reported incidence of allergic reactions to penicillin ranges from 0.7 to 10 percent (see WARNINGS). Sensitization is usually the result of treatment, but some individuals have had immediate reactions to penicillin when first treated. In such cases, it is thought that the patients may have had prior exposure to the drug via trace amounts present in milk or vaccines. Two types of allergic reactions to penicillins are noted clinically, immediate and delayed.

Immediate reactions usually occur within 20 minutes of administration and range in severity from urticaria and pruritus to angioedema, laryngospasm, bronchospasm, hypotension, vascular collapse, and death. Such immediate anaphylactic reactions are very rare (see WARNINGS) and usually occur after parenteral therapy but have occurred in patients receiving oral therapy. Another type of immediate reaction, an accelerated reaction, may occur between 20 minutes and 48 hours after administration and may include urticaria, pruritus, and fever.

Although laryngeal edema, laryngospasm, and hypotension occasionally occur, fatality is uncommon. Delayed allergic reactions to penicillin therapy usually occur after 48 hours and sometimes as late as 2 to 4 weeks after initiation of therapy. Manifestations of this type of reaction include serum sickness-like symptoms (i.e., fever, malaise, urticaria, myalgia, arthralgia, abdominal pain) and various skin rashes. Nausea, vomiting, diarrhea, stomatitis, black or hairy tongue, and other symptoms of gastrointestinal irritation may occur, especially during oral penicillin therapy.

Local Reactions

Pain, swelling, inflammation, phlebitis, thrombophlebitis, and occasional skin sloughing at the injection site have occurred with intravenous administration of nafcillin. (See DOSAGE AND ADMINISTRATION) Severe tissue necrosis with sloughing secondary to subcutaneous extravasation of nafcillin has been reported.

Nervous System Reactions

Neurotoxic reactions similar to those observed with penicillin G could occur with large intravenous or intraventricular doses of nafcillin especially in patients with concomitant hepatic insufficiency and renal dysfunction. (See PRECAUTIONS).

Urogenital Reactions

Renal tubular damage and interstitial nephritis have been associated with the administration of nafcillin. Manifestations of this reaction may include rash, fever, eosinophilia, hematuria, proteinuria, and renal insufficiency.

Hepatic Reactions

Elevation of liver transaminases and/or cholestasis may occur, especially with administration of high doses of nafcillin.

Gastrointestinal Reactions

Pseudomembranous colitis has been reported with the use of nafcillin. The onset of pseudomembranous colitis symptoms may occur during or after antibiotic treatment (see WARNINGS).

Metabolic Reactions

Agranulocytosis, neutropenia, and bone marrow depression have been associated with the use of nafcillin.

To repor t SUSPECTED ADVERSE EVENTS, contact Onesource at 1-888-217-8103 or www.onesourcecdmo.com or FDA at 1-800-FDA-1088 or
www.fda.gov/medwatch.

OVERDOSAGE

Neurotoxic reactions similar to those observed with penicillin G may arise with intravenous doses of nafcillin especially in patients with concomitant hepatic insufficiency and renal dysfunction (see PRECAUTIONS).

In the case of overdosage, discontinue nafcillin, treat symptomatically and institute supportive measures as required. Hemodialysis does not increase the rate of clearance of nafcillin from the blood.

DOSAGE AND ADMINISTRATION

Nafcillin for Injection is available for intramuscular and intravenous use.

The usual I.V dosage for adults is 500 mg every 4 hours. For severe infections, 1 gram every 4 hours is recommended. Administer slowly over at least 30 to 60 minutes to minimize the risk of vein irritation and extravasation.

RECOMMENDED DOSAGE FOR NAFCILLIN FOR INJECTION, USP
Drug | Adults | Infants and Children <40 kg (88 lbs) | Other Recommendations
Nafcillin | 500 mg IM every 4 to 6 hours. IV every 4 hours | 25 mg/kg IM twice daily | Neonates 10 mg/kg IM twice daily
Nafcillin | 1 gram IM or IV every 4 hours (severe infections)

Bacteriologic studies to determine the causative organisms and their susceptibility to nafcillin should always be performed. Duration of therapy varies with the type and severity of infection as well as the overall condition of the patient; therefore, it should be determined by the clinical and bacteriological response of the patient. In severe staphylococcal infections, therapy with nafcillin should be continued for at least 14 days. The treatment of endocarditis and osteomyelitis may require a longer duration of therapy.

No dosage alterations are necessary for patients with renal dysfunction, including those on hemodialysis. Hemodialysis does not accelerate nafcillin clearance from the blood.

With intravenous administration, particularly in elderly patients, care should be taken because of the possibility of thrombophlebitis.

Parenteral drug products should be inspected visually for particulate matter and discoloration prior to administration whenever solution and container permit. Do not add supplementary medication to Nafcillin.

DIRECTIONS FOR USE

For Intramuscular Use

Reconstitute with Sterile Water for Injection, USP, 0.9% Sodium Chloride Injection, USP or Bacteriostatic Water for Injection, USP (with benzyl alcohol or parabens); add 3.4 mL to the 1 g vial for 4 mL resulting solution and 6.6 mL to the 2 g vial for 8 mL resulting solution. All reconstituted vials have a concentration of 250 mg per mL.

The clear solution should be administered by deep intragluteal injection immediately after reconstitution.

Reconstituted Stability

Reconstitute with the required amount of Sterile Water for Injection, USP, 0.9% Sodium Chloride Injection, USP or Bacteriostatic Water for Injection, USP (with benzyl alcohol or parabens). The resulting solutions are stable for 3 days at room temperature or 7 days under refrigeration and 90 days frozen.

For Direct Intravenous Use

The required amount of drug should be diluted in 15 to 30 mL of Sterile Water for Injection, USP or Sodium Chloride Injection, USP and injected over a 5- to 10- minute period. This may be accomplished through the tubing of an intravenous infusion if desirable.

For Administration by Intravenous Drip

Reconstitute as directed above (For Intravenous Use) prior to diluting with intravenous solution.

STABILITY PERIODS FOR NAFCILLIN FOR INJECTION, USP*
Concentration; mg/mL | Sterile; water for Injection, USP | Sodium Chloride Injection USP | Sodium Lactate Solution USP (M/6 Molar) | Dextrose injection USP (5%) | Dextrose and sodium chloride injection USP (5% Dextrose and 0.45% Sodium Chloride) | Invert Sugar Injection USP (10%) | Lactated Ringer’s Injection USP
ROOM TEMPERATURE (25° C)
10-200 | 24 Hrs | 24 Hrs
30 |  |  | 24 Hrs
2-30 |  |  |  | 24 Hrs | 24 Hrs
10-30 |  |  |  |  |  | 24 Hrs | 24 Hrs
REFRIGERATION (4° C)
10-200 | 7 Days | 7 Days
10-30 |  |  | 7 Days | 7 Days | 7 Days | 7 Days | 7 Days
FROZEN (-15° C)
250 | 90 Days | 90 Days
10-250 |  |  | 90 Days | 90 Days | 90 Days | 90 Days | 90 Days
*IMPORTANT: This chemical stability information in no way indicates that it would be acceptable practice to use this product well after the preparation time. Good professional practice suggests that a product should be used as soon after preparation as feasible.

Only those solutions listed above should be used for the intravenous infusion of nafcillin sodium, USP. The concentration of the antibiotic should fall within the range specified. The drug concentration and the rate and volume of the infusion should be adjusted so that the total dose of nafcillin is administered before the drug loses its stability in the solution in use.

There is no clinical experience available on the use of this agent in neonates or infants for this route of administration.

This route of administration should be used for relatively short-term therapy (24 to 48 hours) because of the occasional occurrence of thrombophlebitis particularly in elderly patients.

If another agent is used in conjunction with nafcillin therapy, it should not be physically mixed with nafcillin but should be administered separately.

HOW SUPPLIED

Each Nafcillin for Injection, USP vial contains nafcillin sodium equivalent to 1 gram or 2 grams of nafcillin.

NDC | Nafcillin for Injection, USP | Package factor
83270-309-10 | 1 gram vial* | 10s
83270-310-10 | 2 grams vial* | 10s
* Vial stoppers are not made with natural rubber latex.
Store dry powder at 20° to 25°C (68° to 77°F). [See USP Controlled Room Temperature.]

Manufactured by:

OneSource Specialty Pharma Limited
Beta Lactam Division, Bengaluru-560076, India.

Rev. 02/2026

Package/Label Display Panel

Vial Label:

NDC 83270-309-01

Rx only

Nafcillin for Injection, USP

(1 gram per vial)

Sterile

Buffered for Intramuscular and Intravenous use

Carton Label:

NDC 83270-309-10

Rx only

Nafcillin for Injection, USP

(1 gram per vial)

Sterile

Buffered for Intramuscular and Intravenous use

Vial Label:

NDC 83270-310-01

Rx only

Nafcillin for Injection, USP

(2 grams per vial)

Sterile

Buffered for Intramuscular and Intravenous use

Carton Label:

NDC 83270-310-10

Rx only

Nafcillin for Injection, USP

(2 grams per vial)

Sterile

Buffered for Intramuscular and Intravenous use